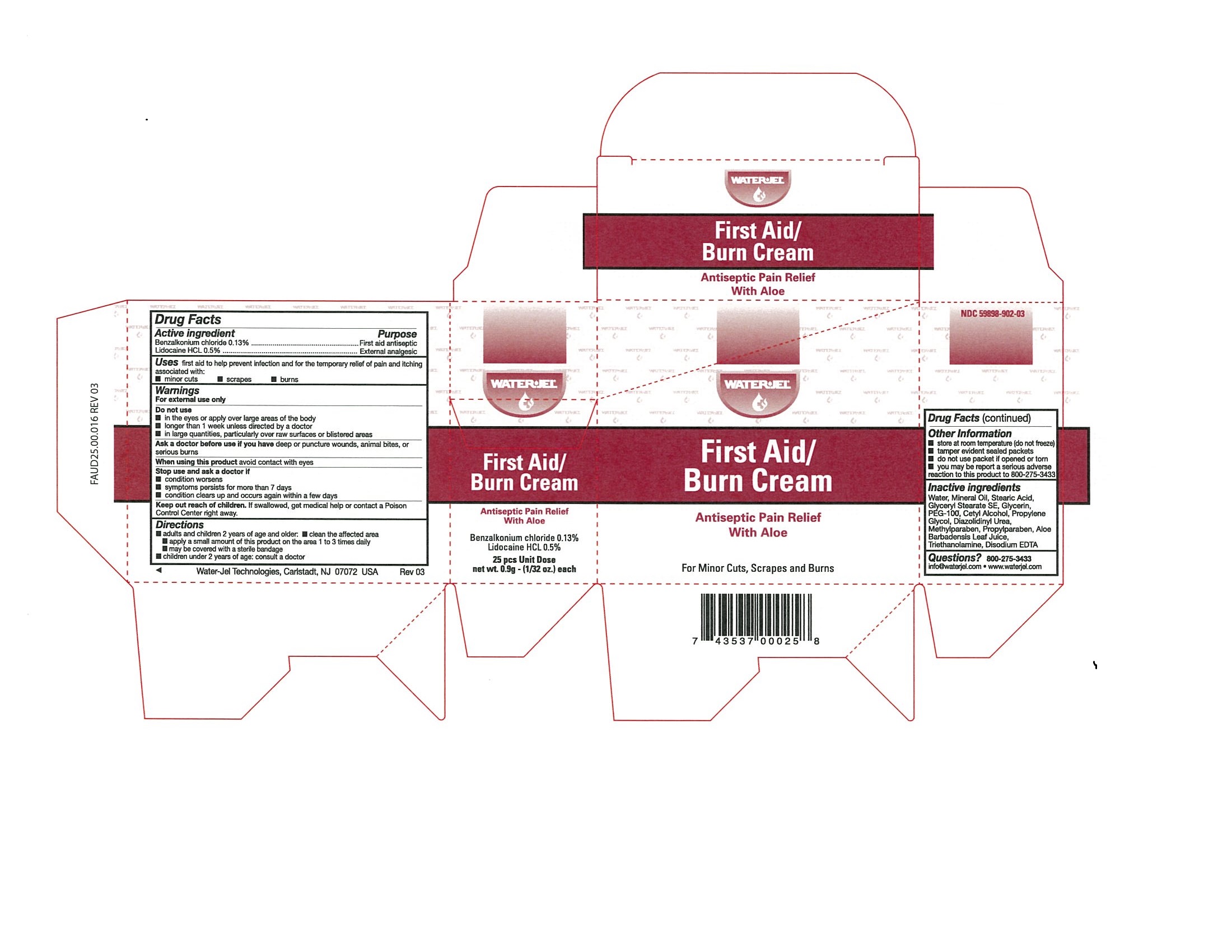 DRUG LABEL: First Aid Burn
NDC: 59898-902 | Form: CREAM
Manufacturer: Water-Jel Technologies
Category: otc | Type: HUMAN OTC DRUG LABEL
Date: 20171130

ACTIVE INGREDIENTS: LIDOCAINE HYDROCHLORIDE 0.5 g/100 g; BENZALKONIUM CHLORIDE 0.13 g/100 g
INACTIVE INGREDIENTS: EDETATE DISODIUM; LIGHT MINERAL OIL; STEARIC ACID; PEG-100 STEARATE; CETYL ALCOHOL; TROLAMINE; GLYCERIN; METHYLPARABEN; PROPYLENE GLYCOL; DIAZOLIDINYL UREA; ALOE VERA LEAF; WATER; PROPYLPARABEN; GLYCERYL MONOSTEARATE

First Aid Burn Cream

Active ingredients

Benzalkonium chloride 0.13%

Lidocaine HCl 0.5%

Purpose

First Aid antiseptic

External analgesic

Uses

first aid to help prevent infection and for the temporary relief of pain and itching associated with

- minor cuts

- scrapes

- burns

Warnings

For external use only

Do not use

- in the eyes or apply over large areas of the body
- longer than 1 week unless directed by a doctor
- in large quantities, particularly over raw surfaces or blistered areas

Ask a doctor before use if you have

deep or puncture wounds, animal bites, or serious burns

When using this product

avoid contact with eyes

Stop use and ask a doctor if

- condition worsens
- symptoms persist for more than 7 days
- condition clears up and occurs again within a few days

Keep out of the reach of children

If swallowed, get medical help or contact a Poison Control Center right away.

Directions

- adults and children 2 years of age and older:
- clean the affected area
- apply a small amount of this product on the area 1 to 3 times daily
- may be covered with a sterile bandage
- children under 2 years of age: consult a doctor

Other information

- store at room temperature (do not freeze)
- tamper evident sealed packets
- do not use if packet is opened or torn
- you may report a serious reaction to this product to 800-275-3433

Inactive ingredients

water, mineral oil, stearic acid, glyceryl stearate se, glycerin, Peg-100, cetyl alcohol, propylene glycol, diazolidinyl urea, methylparaben, propylparaben, aloe barbadensis leaf juice, triethanolamine, disodium EDTA

Questions?

800-275-3433 info@waterjel.com www.waterjel.com